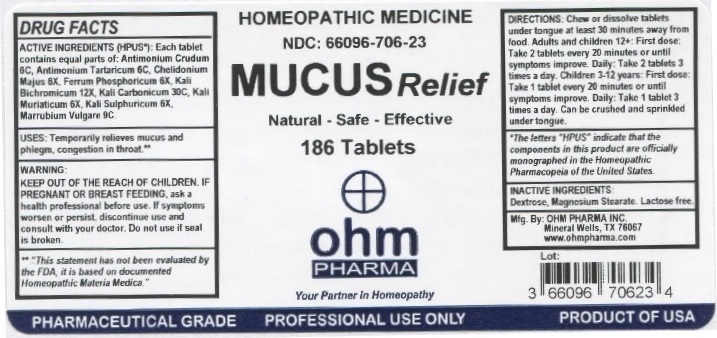 DRUG LABEL: OHM Mucus Relief
NDC: 66096-706 | Form: TABLET, CHEWABLE
Manufacturer: OHM PHARMA INC.
Category: homeopathic | Type: HUMAN OTC DRUG LABEL
Date: 20210111

ACTIVE INGREDIENTS: ANTIMONY TRISULFIDE 6 [hp_C]/1 1; ANTIMONY POTASSIUM TARTRATE 6 [hp_C]/1 1; CHELIDONIUM MAJUS 6 [hp_X]/1 1; FERROSOFERRIC PHOSPHATE 6 [hp_X]/1 1; POTASSIUM DICHROMATE 12 [hp_X]/1 1; POTASSIUM CARBONATE 30 [hp_C]/1 1; POTASSIUM CHLORIDE 6 [hp_X]/1 1; POTASSIUM SULFATE 6 [hp_X]/1 1; MARRUBIUM VULGARE 9 [hp_C]/1 1
INACTIVE INGREDIENTS: DEXTROSE; MAGNESIUM STEARATE

OHM Mucus Relief

ACTIVE INGREDIENT

ACTIVE INGREDIENTS (HPUS*): Each tablet contains equal parts of: Antimonium Crudum 6C, Antimonium Tartaricum 6C, Chelidonium Majus 6X, Ferrum Phosphoricum 6X, Kali Carboonicum 30C, Kali Muriaticum 6X, Kali Sulphuricum 6X, Marrubium Vulgare 9C.

* *The letters "HPUS" indicate that the components in this product are officially monographed in the Homeopathic Pharmacopeia of the United States.

INDICATIONS AND USAGE

USES: Temporarily relieves mucus and phlegm, congestion in throat.**

**This statement has not been evaluated by the FDA. It is based on documented Homeopathic Materia Medica.

WARNINGS

WARNING: IF PREGNANT OR BREAST FEEDING, ask a health professional before use. If symptoms worsen or persist, discontinue use and consult with your doctor.

- KEEP OUT OF REACH OF CHILDREN.

DOSAGE AND ADMINISTRATION

DIRECTIONS: Chew or dissolve tablets under tongue at least 30 minutes away from food. Adults and children 12+: First dose: Take 2 tablets every 20 minutes or until symptoms improve. Daily: Take 2 tablets 3 times a day. Children 3-12 years: First dose: Take 1 tablet every 20 minutes or until symptoms improve. Daily: Take 1 tablet 3 times a day. Can be crushed and sprinkled under tongue.

Do not use if seal is broken.

INACTIVE INGREDIENTS: Dextrose, Magnesium Stearate, Lactose Free.

QUESTIONS

Mfg. By: OHM PHARMA INC Mineral Wells, TX 76067

www.ohmpharma.com

PACKAGE LABEL

HOMEOPATHIC MEDICINE

NDC: 66096-706-23

MUCUS Relief

Natural - Safe - Effective

186 Tablets

PRODUCT OF USA

PURPOSE

MUCUS Relief